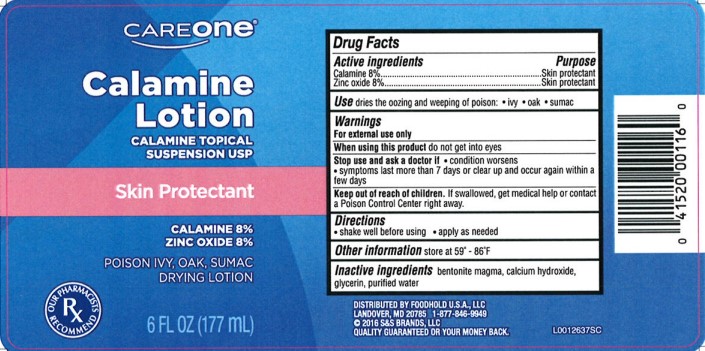 DRUG LABEL: Calamine
NDC: 72476-063 | Form: LOTION
Manufacturer: Retail Business Services, LLC
Category: otc | Type: HUMAN OTC DRUG LABEL
Date: 20260206

ACTIVE INGREDIENTS: FERRIC OXIDE RED 80 mg/1 mL; ZINC OXIDE 80 mg/1 mL
INACTIVE INGREDIENTS: BENTONITE; CALCIUM HYDROXIDE; GLYCERIN; WATER

Care One 063.001/063AA
Calamine Lotion

Active ingredents

Calamine 8%
Zinc oxide 8%

Purpose

Skin Protectant

Use

dries the oozing and weeping of poison:

- ivy
- oak
- sumac

Warnings

For external use only

When using this product

Do not get into eyes

Stop use and ask a doctor if

- condition worsens
- symptoms last more than 7 days or clear up and occur again within a few days

Keep out of reach of children.

If swallowed, get medical help or contact a Poison Control Center right away.

Directions

- shake well before using
- apply as needed

Other information

store at 59⁰ - 86⁰ F

Inactive ingredients

bentonite magma, calcium hydroxide, glycerin, purified water

Adverse Reaction Section

DISTRIBUTED BY FOODHOLD U.S.A., LLC

LANDOVER, MD 20785 1-877-846-9949

2016 S&S BRANDS LLC

QUALITY GUARANTEED OR YOUR MONEY BACK

principal display panel

CAREONE®

Calamine

Lotion

CALAMINE TOPICAL

SUSPENSION USP

Skin Protectant

CALAMINE 8%

ZINC OXIDE 8%

POISON IVY, OAK, SUMACK

DRYING LOTION

OUR PHARMACISTS RECOMMEND

6 FL OZ (177 mL)